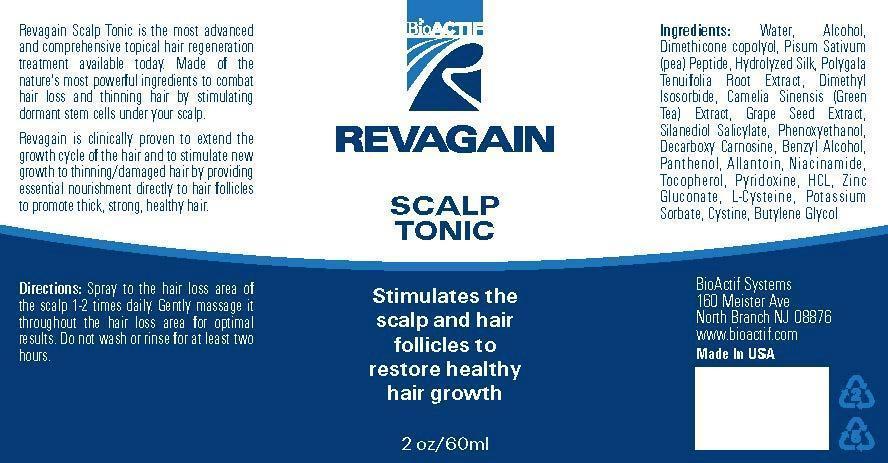 DRUG LABEL: REVAGAIN Scalp Tonic
NDC: 69808-2001 | Form: LIQUID
Manufacturer: AFFINITY GROUP L.L.C.
Category: otc | Type: HUMAN OTC DRUG LABEL
Date: 20150507

ACTIVE INGREDIENTS: ALLANTOIN 0.3 g/100 mL
INACTIVE INGREDIENTS: WATER; PANTHENOL; NIACINAMIDE

Drug Facts

ACTIVE INGREDIENT

allantoin

INACTIVE INGREDIENT

water, alcohol, hydrolyzed silk, dimethyl isosorbide, grape seed ext, green tea ext, panthenol, benzyl alcohol, niacinamide, etc.

PURPOSE

hair growth and loss prevention

keep out or reach of the children

INDICATIONS AND USAGE

spray to the hair loss area of the scalp 1~2 times daily
gently message it throughout the hair loss area for optimal results
do not wash or rinse for at least two hours

WARNINGS

1. Do not use in the following cases(Eczema and scalp wounds)
2.Side Effects
1)Due to the use of this product if rash, irritation, itching and symptopms of hypersnesitivity occur dicontinue use and consult ypur phamacisr or doctor
3.General Precautions
1)If in contact with the eyes, wash out thoroughty with water If the symptoms are servere, seek medical advice immediately
2)This product is for exeternal use only. Do not use for internal use
4.Storage and handling precautions
1)If possible, avoid direct sunlight and store in cool and area of low humidity
2)In order to maintain the quality of the product and avoid misuse
3)Avoid placing the product near fire and store out in reach of children

DOSAGE AND ADMINISTRATION

for external use only